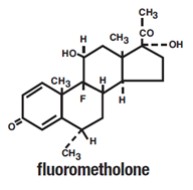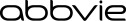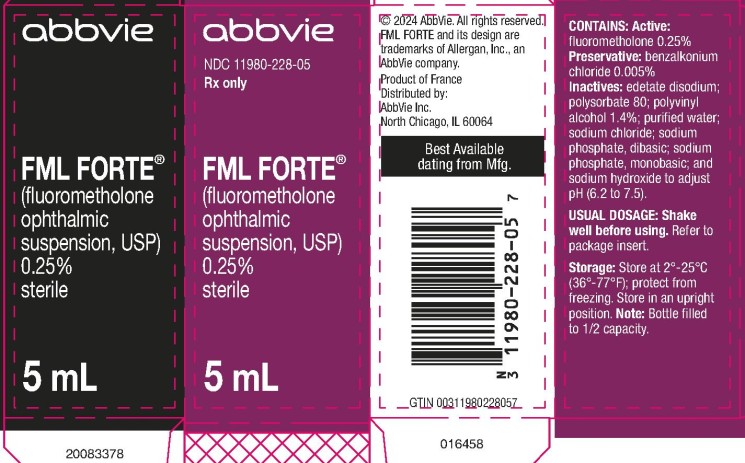 DRUG LABEL: FML FORTE
NDC: 11980-228 | Form: SUSPENSION/ DROPS
Manufacturer: Allergan, Inc.
Category: prescription | Type: HUMAN PRESCRIPTION DRUG LABEL
Date: 20250213

ACTIVE INGREDIENTS: FLUOROMETHOLONE 2.5 mg/1 mL
INACTIVE INGREDIENTS: BENZALKONIUM CHLORIDE; EDETATE DISODIUM; POLYSORBATE 80; POLYVINYL ALCOHOL, UNSPECIFIED; WATER; SODIUM CHLORIDE; SODIUM PHOSPHATE, DIBASIC, UNSPECIFIED FORM; SODIUM PHOSPHATE, MONOBASIC, UNSPECIFIED FORM; SODIUM HYDROXIDE

FML FORTE®
(fluorometholone ophthalmic suspension, USP) 0.25%
sterile
Rx only

DESCRIPTION

FML FORTE® (fluorometholone ophthalmic suspension, USP) 0.25% is a sterile, topical anti-inflammatory agent for ophthalmic use.

Chemical Name

Fluorometholone: 9-Fluoro-11ß, 17-dihydroxy-6α-methylpregna-1,4-diene-3,20-dione

Structural Formula

Contains

Active: fluorometholone 0.25%. Preservative: benzalkonium chloride 0.005%. Inactives: edetate disodium; polysorbate 80; polyvinyl alcohol 1.4%; purified water; sodium chloride; sodium phosphate, dibasic; sodium phosphate, monobasic; and sodium hydroxide to adjust pH. FML FORTE® suspension is formulated with a pH from 6.2 to 7.5.

CLINICAL PHARMACOLOGY

Corticosteroids inhibit the inflammatory response to a variety of inciting agents and probably delay or slow healing. They inhibit the edema, fibrin deposition, capillary dilation, leukocyte migration, capillary proliferation, fibroblast proliferation, deposition of collagen, and scar formation associated with inflammation.

There is no generally accepted explanation for the mechanism of action of ocular corticosteroids. However, corticosteroids are thought to act by the induction of phospholipase A2 inhibitory proteins, collectively called lipocortins. It is postulated that these proteins control the biosynthesis of potent mediators of inflammation such as prostaglandins and leukotrienes by inhibiting the release of their common precursor, arachidonic acid. Arachidonic acid is released from membrane phospholipids by phospholipase A2.

Corticosteroids are capable of producing a rise in intraocular pressure. In clinical studies of documented steroid-responders, fluorometholone demonstrated a significantly longer average time to produce a rise in intraocular pressure than dexamethasone phosphate; however, in a small percentage of individuals, a significant rise in intraocular pressure occurred within one week. The ultimate magnitude of the rise was equivalent for both drugs.

INDICATIONS AND USAGE

FML FORTE® suspension is indicated for the treatment of corticosteroid-responsive inflammation of the palpebral and bulbar conjunctiva, cornea and anterior segment of the globe.

CONTRAINDICATIONS

FML FORTE® suspension is contraindicated in most viral diseases of the cornea and conjunctiva, including epithelial herpes simplex keratitis (dendritic keratitis), vaccinia, and varicella, and also in mycobacterial infection of the eye and fungal diseases of ocular structures. FML FORTE® suspension is also contraindicated in individuals with known or suspected hypersensitivity to any of the ingredients of this preparation and to other corticosteroids.

WARNINGS

Prolonged use of corticosteroids may increase intraocular pressure in susceptible individuals, resulting in glaucoma with damage to the optic nerve, defects in visual acuity and fields of vision, and in posterior subcapsular cataract formation. Prolonged use may also suppress the host immune response and thus increase the hazard of secondary ocular infections.

Various ocular diseases and long-term use of topical corticosteroids have been known to cause corneal and scleral thinning. Use of topical corticosteroids in the presence of thin corneal or scleral tissue may lead to perforation.

Acute purulent infections of the eye may be masked or activity enhanced by the presence of corticosteroid medication.

If this product is used for 10 days or longer, intraocular pressure should be routinely monitored even though it may be difficult in children and uncooperative patients. Steroids should be used with caution in the presence of glaucoma. Intraocular pressure should be checked frequently.

The use of steroids after cataract surgery may delay healing and increase the incidence of bleb formation.

Use of ocular steroids may prolong the course and may exacerbate the severity of many viral infections of the eye (including herpes simplex). Employment of a corticosteroid medication in the treatment of patients with a history of herpes simplex requires great caution; frequent slit lamp microscopy is recommended.

PRECAUTIONS

General

The initial prescription and renewal of the medication order beyond 20 milliliters of FML FORTE® suspension should be made by a physician only after examination of the patient with the aid of magnification, such as slit lamp biomicroscopy and, where appropriate, fluorescein staining. If signs and symptoms fail to improve after two days, the patient should be re-evaluated.

As fungal infections of the cornea are particularly prone to develop coincidentally with long-term local corticosteroid applications, fungal invasion should be suspected in any persistent corneal ulceration where a corticosteroid has been used or is in use. Fungal cultures should be taken when appropriate.

If this product is used for 10 days or longer, intraocular pressure should be monitored (see WARNINGS).

Information for Patients

If inflammation or pain persists longer than 48 hours or becomes aggravated, the patient should be advised to discontinue use of the medication and consult a physician.

This product is sterile when packaged. To prevent contamination, care should be taken to avoid touching the bottle tip to eyelids or to any other surface. The use of this bottle by more than one person may spread infection. Keep bottle tightly closed when not in use. Keep out of the reach of children.

The preservative in FML FORTE® suspension, benzalkonium chloride, may be absorbed by soft contact lenses. Patients wearing soft contact lenses should be instructed to wait at least 15 minutes after instilling FML FORTE® suspension to insert soft contact lenses.

Carcinogenesis, Mutagenesis, Impairment of Fertility

No studies have been conducted in animals or in humans to evaluate the possibility of these effects with fluorometholone.

Teratogenic effects

Fluorometholone has been shown to be embryocidal and teratogenic in rabbits when administered at low multiples of the human ocular dose. Fluorometholone was applied ocularly to rabbits daily on days 6-18 of gestation, and dose-related fetal loss and fetal abnormalities including cleft palate, deformed rib cage, anomalous limbs and neural abnormalities such as encephalocele, craniorachischisis, and spina bifida were observed. There are no adequate and well-controlled studies of fluorometholone in pregnant women, and it is not known whether fluorometholone can cause fetal harm when administered to a pregnant woman. Fluorometholone should be used during pregnancy only if the potential benefit justifies the potential risk to the fetus.

Nursing Mothers

It is not known whether topical ophthalmic administration of corticosteroids could result in sufficient systemic absorption to produce detectable quantities in human milk. Systemically administered corticosteroids appear in human milk and could suppress growth, interfere with endogenous corticosteroid production, or cause other untoward effects. Because of the potential for serious adverse reactions in nursing infants from fluorometholone, a decision should be made whether to discontinue nursing or to discontinue the drug, taking into account the importance of the drug to the mother.

Pediatric Use

Safety and effectiveness in infants below the age of two years have not been established.

Geriatric Use

No overall differences in safety or effectiveness have been observed between elderly and younger patients.

ADVERSE REACTIONS

Adverse reactions include, in decreasing order of frequency, elevation of intraocular pressure (IOP) with possible development of glaucoma and infrequent optic nerve damage, posterior subcapsular cataract formation, and delayed wound healing.

Although systemic effects are extremely uncommon, there have been rare occurrences of systemic hypercorticoidism after use of topical dermatologic steroids applied to the skin.

Corticosteroid-containing preparations have also been reported to cause acute anterior uveitis and perforation of the globe. Keratitis, conjunctivitis, corneal ulcers, mydriasis, conjunctival hyperemia, loss of accommodation and ptosis have occasionally been reported following local use of corticosteroids.

The development of secondary ocular infection (bacterial, fungal and viral) has occurred. Fungal and viral infections of the cornea are particularly prone to develop coincidentally with long-term applications of steroids. The possibility of fungal invasion should be considered in any persistent corneal ulceration where steroid treatment has been used (see WARNINGS).

Transient burning and stinging upon instillation and other minor symptoms of ocular irritation have been reported with the use of FML FORTE® suspension. Other adverse events reported with the use of fluorometholone include: allergic reactions; foreign body sensation; erythema of eyelid; eyelid edema/eye swelling; eye discharge; eye pain; eye pruritus; lacrimation increased; rash; taste perversion; visual disturbance (blurry vision); and visual field defect.

DOSAGE AND ADMINISTRATION

Shake well before using. Instill one drop into the conjunctival sac two to four times daily. During the initial 24 to 48 hours, the dosing frequency may be increased to one application every four hours. Care should be taken not to discontinue therapy prematurely.

If signs and symptoms fail to improve after two days, the patient should be re-evaluated (see PRECAUTIONS).

The dosing of FML FORTE® suspension may be reduced, but care should be taken not to discontinue therapy prematurely. In chronic conditions, withdrawal of treatment should be carried out by gradually decreasing the frequency of applications.

HOW SUPPLIED

FML FORTE® (fluorometholone ophthalmic suspension, USP) 0.25% is supplied sterile in opaque white LDPE plastic bottles with droppers with pink high impact polystyrene (HIPS) caps as follows:

5 mL in 10 mL bottle NDC 11980-228-05

10 mL in 15 mL bottle NDC 11980-228-10

Storage: Store at 2°-25°C (36°-77°F); protect from freezing. Store in an upright position.

Revised: 2/2025

Distributed by:
AbbVie Inc.
North Chicago, IL 60064

© 2025 AbbVie. All rights reserved.

FML FORTE and its design are trademarks of Allergan, Inc., an AbbVie company.

V3.0USPI228

PRINCIPAL DISPLAY PANEL

NDC 11980-228-05
Rx only
FML FORTE®
(fluorometholone
ophthalmic
suspension, USP)
0.25%
Sterile
5 mL